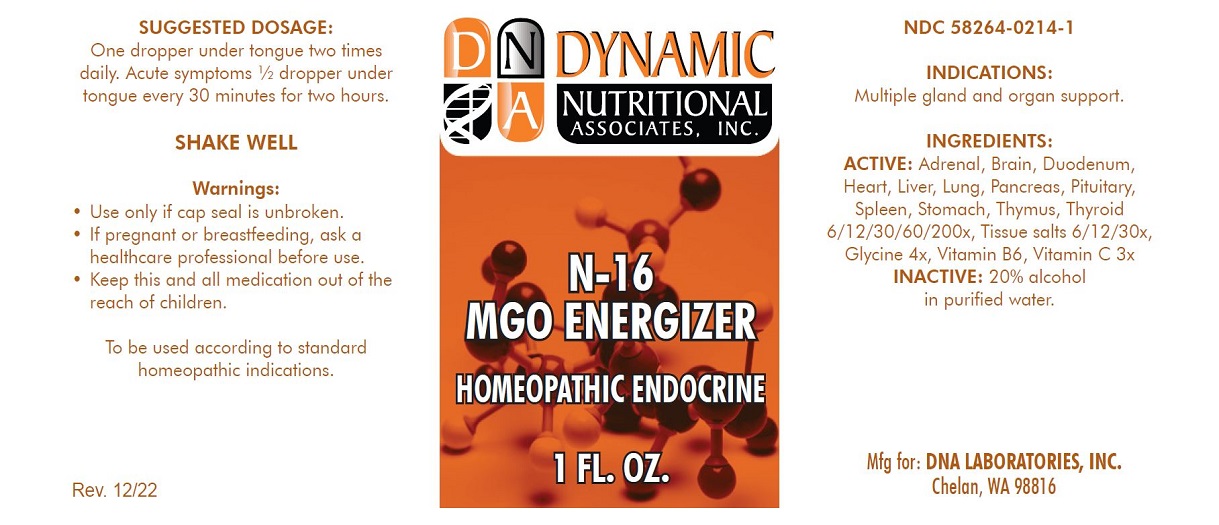 DRUG LABEL: N-16
NDC: 58264-0214 | Form: SOLUTION
Manufacturer: DNA Labs, Inc.
Category: homeopathic | Type: HUMAN OTC DRUG LABEL
Date: 20250109

ACTIVE INGREDIENTS: BOS TAURUS ADRENAL GLAND 200 [hp_X]/1 mL; BOS TAURUS THYMUS 200 [hp_X]/1 mL; SUS SCROFA SPLEEN 200 [hp_X]/1 mL; TRIPE 200 [hp_X]/1 mL; BOS TAURUS PITUITARY GLAND, POSTERIOR 200 [hp_X]/1 mL; MAMMAL LIVER 200 [hp_X]/1 mL; SUS SCROFA LUNG 200 [hp_X]/1 mL; BEEF HEART 200 [hp_X]/1 mL; PORK BRAIN 200 [hp_X]/1 mL; SUS SCROFA DUODENUM 200 [hp_X]/1 mL; SUS SCROFA PANCREAS 200 [hp_X]/1 mL; THYROID, UNSPECIFIED 200 [hp_X]/1 mL; PYRIDOXINE HYDROCHLORIDE 3 [hp_X]/1 mL; ASCORBIC ACID 3 [hp_X]/1 mL; GLYCINE 4 [hp_X]/1 mL; CALCIUM FLUORIDE 30 [hp_X]/1 mL; TRIBASIC CALCIUM PHOSPHATE 30 [hp_X]/1 mL; CALCIUM SULFATE ANHYDROUS 30 [hp_X]/1 mL; FERROSOFERRIC PHOSPHATE 30 [hp_X]/1 mL; POTASSIUM CHLORIDE 30 [hp_X]/1 mL; DIBASIC POTASSIUM PHOSPHATE 30 [hp_X]/1 mL; POTASSIUM SULFATE 30 [hp_X]/1 mL; MAGNESIUM PHOSPHATE, DIBASIC TRIHYDRATE 30 [hp_X]/1 mL; SODIUM CHLORIDE 30 [hp_X]/1 mL; SODIUM PHOSPHATE, DIBASIC, HEPTAHYDRATE 30 [hp_X]/1 mL; SODIUM SULFATE 30 [hp_X]/1 mL; SILICON DIOXIDE 30 [hp_X]/1 mL
INACTIVE INGREDIENTS: ALCOHOL; WATER

N-16

NDC 58264-0214-1

INDICATIONS

PURPOSE

Multiple gland and organ support.

INGREDIENTS

INACTIVE INGREDIENT

Adrenal, Brain, Duodenum, Heart, Liver, Lung, Pancreas, Pituitary, Spleen, Stomach, Thymus, Thyroid 6/12/30/60/200x, Tissue salts 6/12/30x, Glycine 4x, Vitamin B6, Vitamin C 3x, 20% alcohol in purified water.

SUGGESTED DOSAGE

One dropper under tongue two times daily. Acute symptoms ½ dropper under tongue every 30 minutes for two hours.

STORAGE AND HANDLING

SHAKE WELL

Warnings

- Use only if cap seal is unbroken.

PREGNANCY OR BREAST FEEDING

- As with drugs if you are pregnant or nursing a baby seek professional advice before using this product.

KEEP OUT OF REACH OF CHILDREN

- Keep this and all medication out of the reach of children.

To be used according to standard homeopathic indications.

PRINCIPAL DISPLAY PANEL - 1 FL. OZ. Bottle Label

DYNAMIC
NUTRITIONAL
ASSOCIATES, INC.

N-16
MGO ENERGIZER

HOMEOPATHIC ENDOCRINE

1 FL. OZ.